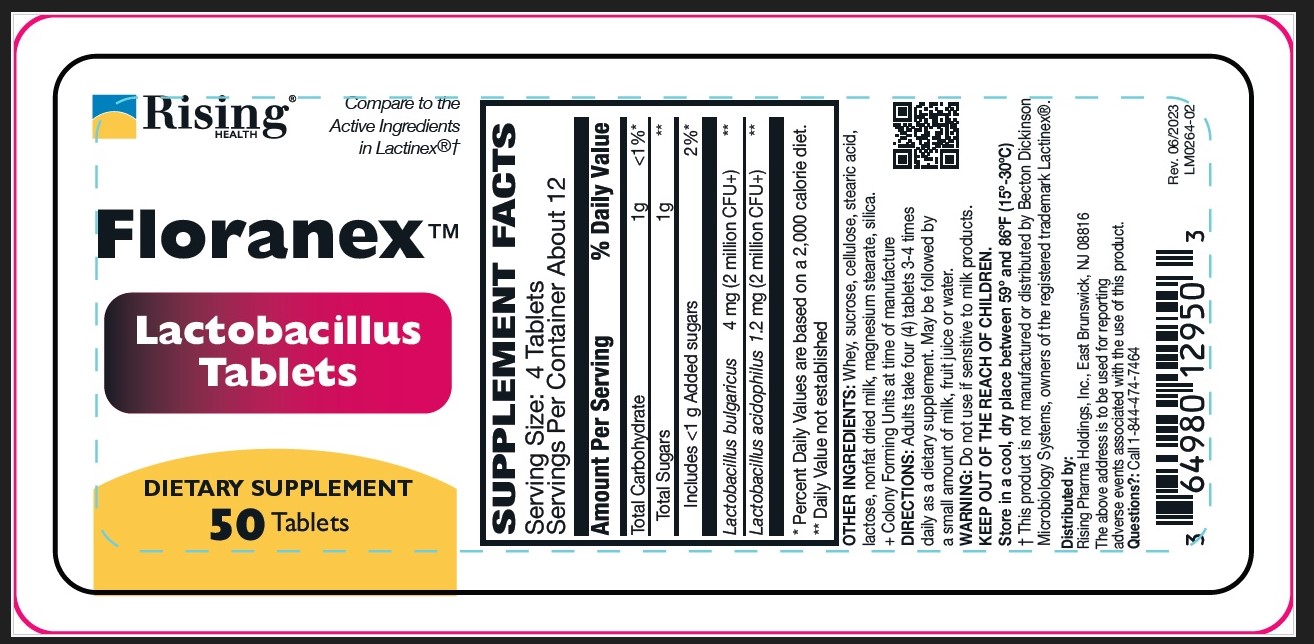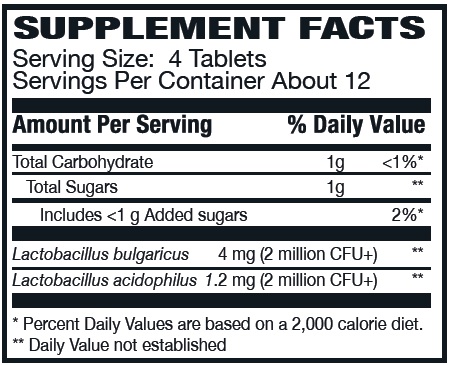 DRUG LABEL: Floranex
NDC: 64980-129 | Form: TABLET
Manufacturer: Rising Pharma Holdings, Inc.
Category: other | Type: DIETARY SUPPLEMENT
Date: 20250619

ACTIVE INGREDIENTS: LACTOBACILLUS ACIDOPHILUS 1.2 mg/1 1; LACTOBACILLUS DELBRUECKII BULGARICUS 4 mg/1 1
INACTIVE INGREDIENTS: SUCROSE; CELLULOSE, MICROCRYSTALLINE; WHEY; MAGNESIUM STEARATE; STEARIC ACID; LACTOSE; SILICA; SKIM MILK

Floranex™, DIETARY SUPPLEMENT, 50 Tablets

STATEMENT OF IDENTITY

OTHER INGREDIENTS: Whey, sucrose, cellulose, stearic acid, lactose, nonfat dried milk, magnesium stearate, silica.
+ Colony Forming Units at time of manufacture

DOSAGE AND ADMINISTRATION

DIRECTIONS: Adults take four (4) tablets 3-4 times daily as a dietary supplement. May be followed by a small amount of milk, fruit juice or water.

WARNINGS

WARNING: Do not use if sensitive to milk products.

SAFE HANDLING WARNING

KEEP OUT OF THE REACH OF CHILDREN.

Store in a cool, dry place between 59º and 86ºF (15º-30ºC)

† This product is not manufactured or distributed by Becton Dickinson Microbiology Systems, owners of the registered trademark Lactinex®.

Distributed by:

Rising Pharma Holdings, Inc., East Brunswick, NJ 08816

The above address is to be used for reporting adverse events associated with the use of this product.

Questions?: Call 1-844-474-7464

Rev. 06/2023
LM0264-02

PACKAGE LABEL

Floranex™

DIETARY SUPPLEMENT

50 Tablets

Bottle label (64980-129-50)